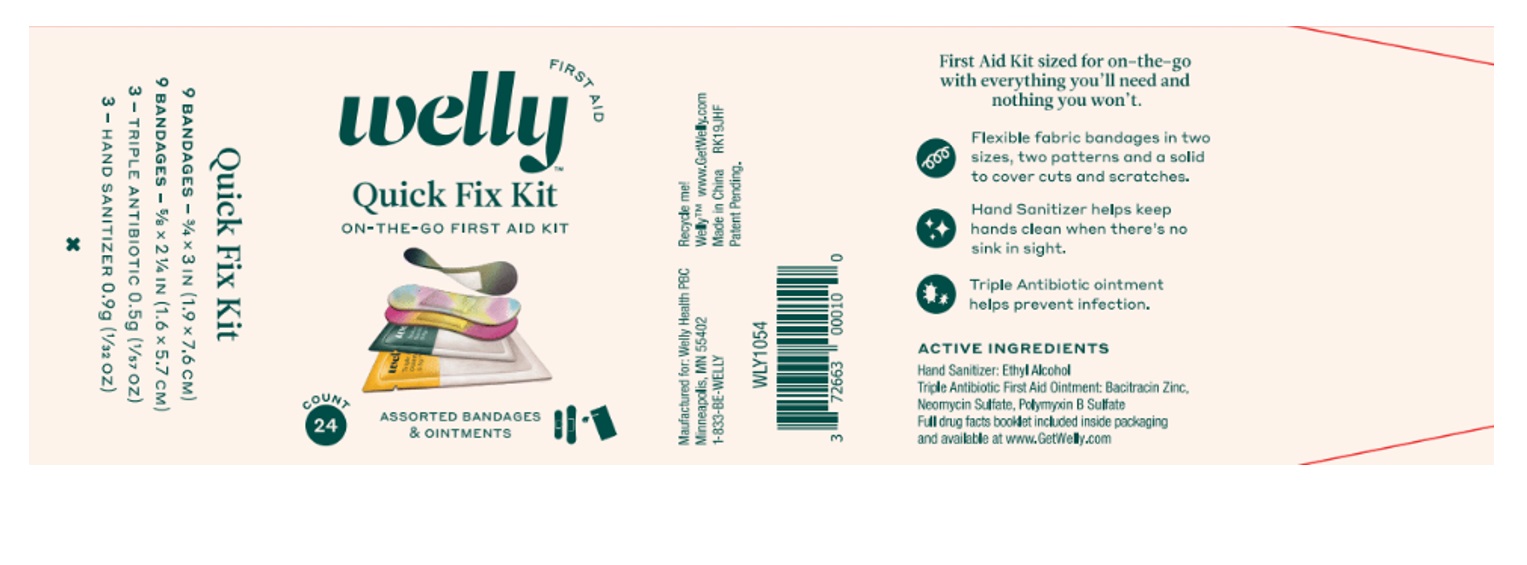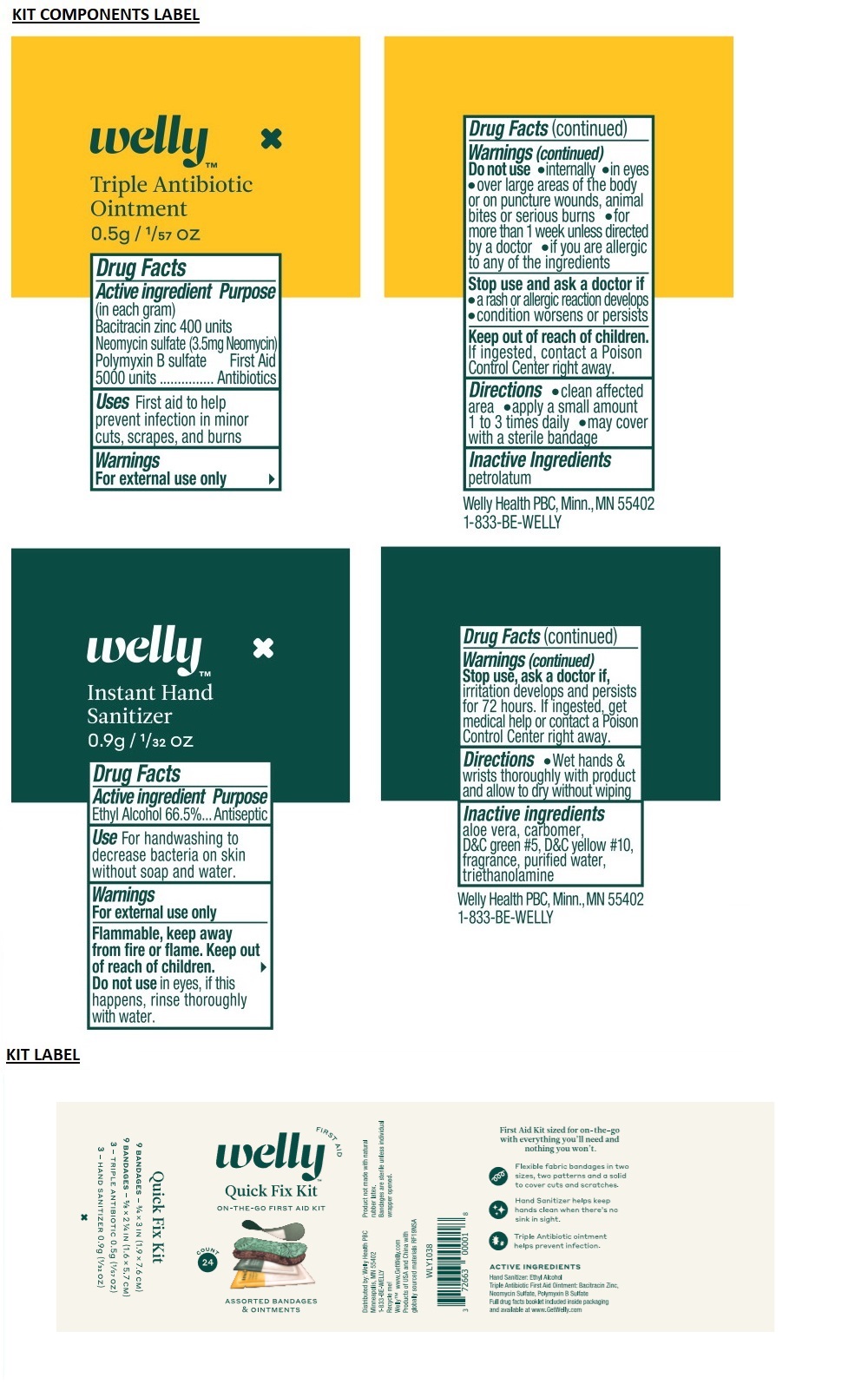 DRUG LABEL: Welly Quick Fix Kit
NDC: 72663-000 | Form: KIT | Route: TOPICAL
Manufacturer: Welly Health PBC
Category: otc | Type: HUMAN OTC DRUG LABEL
Date: 20211231

ACTIVE INGREDIENTS: ALCOHOL 666 mg/1 mL; BACITRACIN ZINC 6 mg/1 mL; NEOMYCIN SULFATE 3.5 mg/1 mL; POLYMYXIN B SULFATE 0.77 mg/1 mL
INACTIVE INGREDIENTS: ALOE VERA LEAF; CARBOMER INTERPOLYMER TYPE A (ALLYL SUCROSE CROSSLINKED); D&C GREEN NO. 5; D&C YELLOW NO. 10; WATER; TROLAMINE; PETROLATUM

Welly Quick Fix Kit

Triple Antibiotic Ointment

Drug Facts

Active ingredient (in each gram)

Bacitracin zinc 400 units

Neomycin sulfate (3.5mg Neomycin)

Polymyxin B sulfate 5000 units

Purpose

First Aid Antibiotics

Uses

First aid to help prevent infection in minor cuts, scrapes and burns

Warnings

For external use only

Do not use

- internally
- in eyes
- over large areas of the body or on puncture wounds, animal bites or serious burns
- for more than 1 week unless directed by a doctor
- if you are allergic to any of the ingredients

Stop use and ask a doctor if

- a rash or allergic reaction develops
- condition worsens or persists

Keep out of reach of children. If ingested, contact a Poison Control Center right away.

Directions

- clean affected area
- apply a small amount 1 to 3 times daily
- may cover with a sterile bandage

Inactive Ingredients

petrolatum

Instant Hand Sanitizer Gel

Drug Facts

Active ingredient

Ethyl Alcohol 66.5%

Purpose

Antiseptic

Use

For handwashing to decrease bacteria on skin without soap and water.

Warnings

For external use only

Flammable, keep away from fire or flame.

Do not use in eyes, if this happens, rinse thoroughly with water.

Stop use, ask a doctor if, irritation develops and persists for 72 hours.

Keep out of reach of children. If ingested, get medical help or contact a Poison Control Center right away.

Directions

- Wet hands & wrists thoroughly with product and allow to dry without wiping

Inactive ingredients

aloe vera, carbomer, D&C green #5, D&C yellow #10, fragrance, purified water, triethanolamine

ON-THE-GO FIRST AID KIT

ASSORTED BANDAGES & OINTMENTS

First Aid Kit sized for on-the-go with everything you'll need and nothing you won't.

- Flexible fabric bandages in two sizes, two patterns and a solid to cover cuts and scratches.
- Hand Sanitizer helps keep hands clean when there's no sink in sight.
- Triple Antibiotic ointment helps prevent infection.

Product not made with natural rubber latex.
Bandages are sterile unless individual wrapper opened.

Quick Fix Kit

9 BANDAGES - 3/4 x 3 IN (1.9 x 7.6 CM)

9 BANDAGES - 5/8 X 2 1/4 IN (1.6 X 5.7 CM)

3 - TRIPLE ANTIBIOTIC 0.5g (1/57 OZ)

3 - HAND SANITIZER 0.9g (1/32 OZ)

Distributed by: Welly Health PBC
Minneapolis, MN 55402
1-833-BE-WELLY

Recycle me!

WellyTM www.GetWelly.com